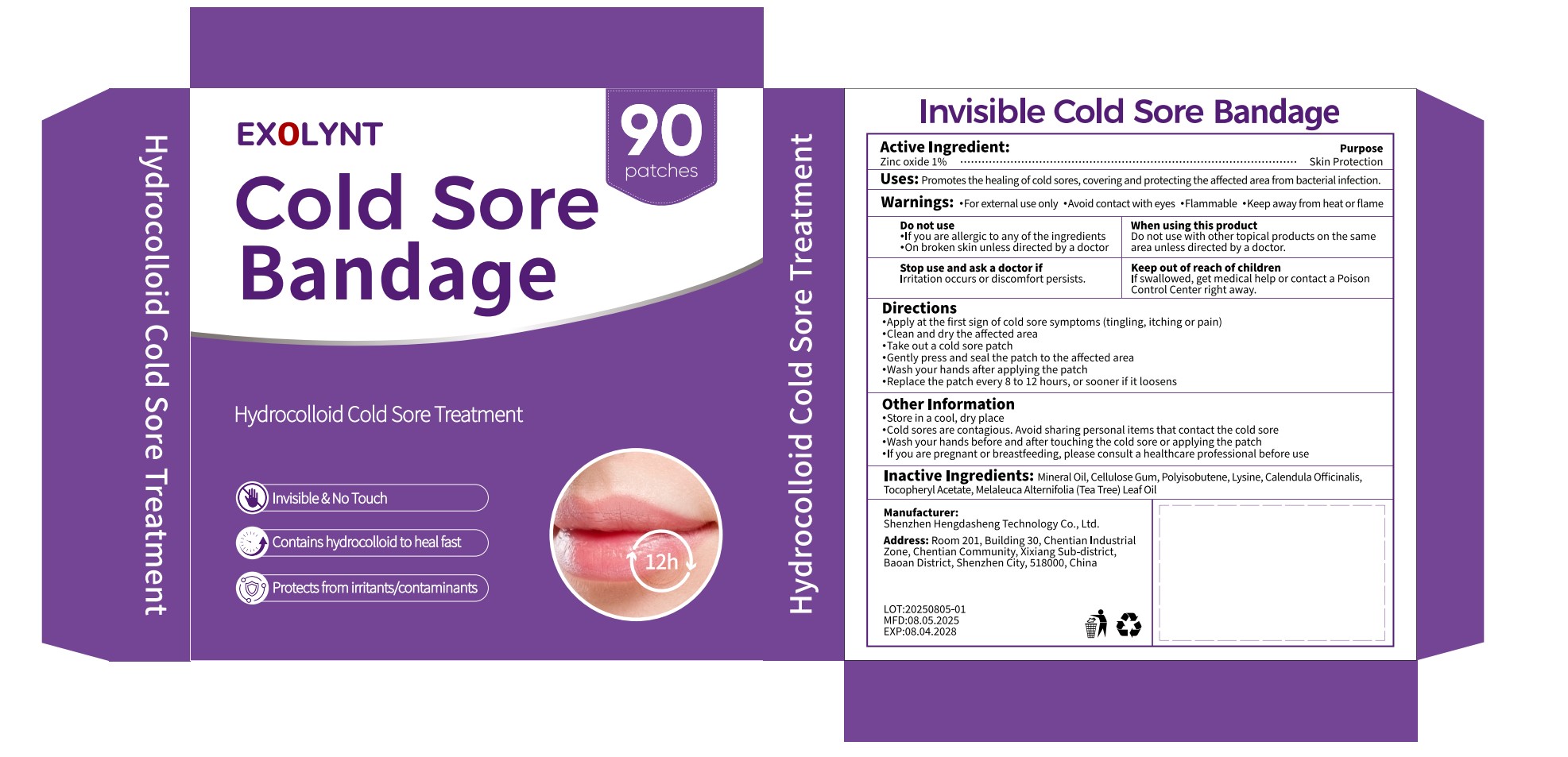 DRUG LABEL: Cold Sore Bandage
NDC: 87308-003 | Form: PATCH
Manufacturer: Shenzhen Hengdasheng Technology Co., Ltd
Category: otc | Type: HUMAN OTC DRUG LABEL
Date: 20260117

ACTIVE INGREDIENTS: ZINC OXIDE 1 U/100 U
INACTIVE INGREDIENTS: MINERAL OIL; CELLULOSE GUM; POLYISOBUTYLENE (1000 MW); LYSINE; ALPHA-TOCOPHEROL ACETATE; MELALEUCA ALTERNIFOLIA (TEA TREE) LEAF OIL

87308-003
Cold Sore Bandage

Active Ingredient(s)

Zinc oxide 1%

Purpose

Skin Protection

Use

Promotes the healing of cold sores, covering and protecting the affected area from bacterial infection.

Warnings

For external use only

Avoid contact with eyes

Flammable

Keep away from heat or flame

Do not use

If you are allergic to any of the ingredients
On broken skin unless directed by a doctor

Do not use with other topical products on the same area unless directed by a doctor.

STOP USE

Irritation occurs or discomfort persists.

KEEP OUT OF REACH OF CHILDREN

If swallowed, get medical help or contact a Poison Control Center right away.

Directions

Apply at the first sign of cold sore symptoms (tingling, itching or pain)

Clean and dry the affected area

Take out a cold sore patch

Gently press and seal the patch to the affected area

Wash your hands after applying the patch

Replace the patch every 8 to 12 hours, or sooner if it loosens

Other information

Store in a cool, dry place

Cold sores are contagious. Avoid sharing personal items that contact the cold sore

Wash your hands before and after touching the cold sore or applying the patch

If you are pregnant or breastfeeding, please consult a healthcare professional before use

Inactive ingredients

Mineral Oil, Cellulose Gum, Polyisobutene, Lysine, Calendula Officinalis,Tocopheryl Acetate, Melaleuca Alternifolia (Tea Tree) Leaf Oil